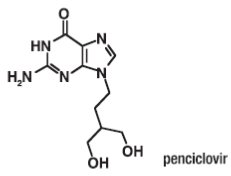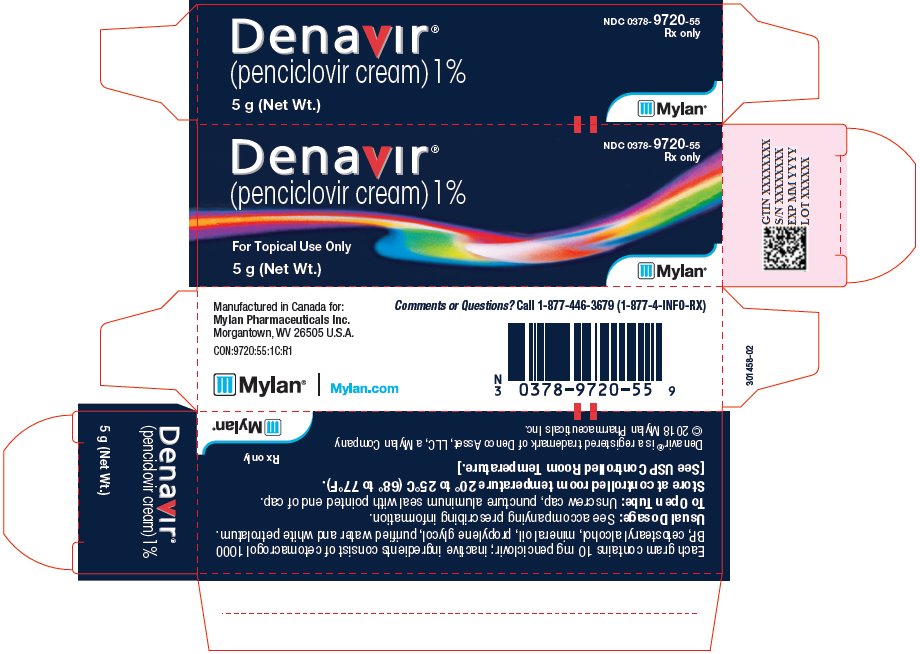 DRUG LABEL: Denavir
NDC: 0378-9720 | Form: CREAM
Manufacturer: Mylan Pharmaceuticals Inc.
Category: prescription | Type: HUMAN PRESCRIPTION DRUG LABEL
Date: 20181126

ACTIVE INGREDIENTS: PENCICLOVIR 10 mg/1 g
INACTIVE INGREDIENTS: CETOSTEARYL ALCOHOL; MINERAL OIL; POLYOXYL 20 CETOSTEARYL ETHER; PROPYLENE GLYCOL; WATER; PETROLATUM

HIGHLIGHTS OF PRESCRIBING INFORMATION

These highlights do not include all the information needed to use DENAVIR® safely and effectively. See full prescribing information for DENAVIR®.
DENAVIR® (penciclovir) Cream, for topical administration
Initial U.S. Approval: 1996

1 INDICATIONS AND USAGE

DENAVIR® is a deoxynucleoside analog HSV DNA polymerase inhibitor indicated for the treatment of recurrent herpes labialis (cold sores) in adults and pediatric patients12 years of age and older. (1)

2 DOSAGE AND ADMINISTRATION

- Apply DENAVIR every 2 hours during waking hours for a period of 4 days (2).
- Start treatment as early as possible (i.e., during the prodrome or when lesions appear). (2)

3 DOSAGE FORMS AND STRENGTHS

- Topical cream containing 1% penciclovir (3).

4 CONTRAINDICATIONS

- Contraindicated in patients with known hypersensitivity to the product or any of its components. (4)

5 WARNINGS AND PRECAUTIONS

- Only for topical use of herpes labialis on the lips and face. (5)

6 ADVERSE REACTIONS

- One or more local skin reactions were reported by 3% of the subjects treated with DENAVIR and 4% of placebo-treated patients. (6.1)

To report SUSPECTED ADVERSE REACTIONS, contact Mylan at 1-877-446-3679 (1-877-4-INFO-RX) or FDA at 1-800-FDA-1088 or www.fda.gov/medwatch.

FULL PRESCRIBING INFORMATION

1 INDICATIONS AND USAGE

DENAVIR is a deoxynucleoside analog HSV DNA polymerase inhibitor indicated for the treatment of recurrent herpes labialis (cold sores) in adults and children 12 years of age or older.

2 DOSAGE AND ADMINISTRATION

Apply DENAVIR every 2 hours during waking hours for a period of 4 days. Start treatment as early as possible (i.e., during the prodrome or when lesions appear).

3 DOSAGE FORMS AND STRENGTHS

DENAVIR is supplied in a 5 gram tube containing 10 mg of penciclovir per gram in a cream base, which is equivalent to 1% (w/w).

4 CONTRAINDICATIONS

DENAVIR is contraindicated in patients with known hypersensitivity to the product or any of its components.

5 WARNINGS AND PRECAUTIONS

5.1 General

DENAVIR should only be used on herpes labialis on the lips and face. Because no data are available, application to human mucous membranes is not recommended. Particular care should be taken to avoid application in or near the eyes since it may cause irritation. Lesions that do not improve or that worsen on therapy should be evaluated for secondary bacterial infection. The effect of DENAVIR has not been established in immunocompromised patients.

6 ADVERSE REACTIONS

6.1 Clinical Studies

Because clinical trials are conducted under widely varying conditions, adverse reaction rates observed in the clinical trials of a drug cannot be directly compared to rates in the clinical trials of another drug and may not reflect the rates observed in clinical practice.

In two double-blind, placebo-controlled trials, 1,516 patients were treated with DENAVIR (penciclovir cream) and 1,541 with placebo. One or more local adverse reactions were reported by 3% of the patients treated with DENAVIR and 4% of placebo-treated patients. The rates of reported local adverse reactions are shown in Table 1.

TABLE 1 - Local Adverse Reactions Reported in Phase III Trials
 | Penciclovir; N=1,516; % | Placebo; N=1,541; %
Application site reaction | 1 | 2
Hypesthesia/Local anesthesia | <1 | <1
Taste perversion | <1 | <1
Rash (erythematous) | <1 | <1

Two studies, enrolling 108 healthy subjects, were conducted to evaluate the dermal tolerance of 5% penciclovir cream (a 5-fold higher concentration than the commercial formulation) compared to vehicle using repeated occluded patch testing methodology. The 5% penciclovir cream induced mild erythema in approximately one-half of the subjects exposed, an irritancy profile similar to the vehicle control in terms of severity and proportion of subjects with a response. No evidence of sensitization was observed.

6.2 Post-Marketing Experience

The following adverse reactions have been identified during post-approval use of DENAVIR. Because these reactions are reported voluntarily from a population of uncertain size, it is not always possible to reliably estimate their frequency or establish a causal relationship to drug exposure.

The following events have been identified from worldwide post-marketing use of DENAVIR in treatment of recurrent herpes labialis (cold sores) in adults. These events have been chosen for inclusion due to a combination of their seriousness, frequency of reporting, or potential causal connection to DENAVIR.

General: Headache, oral/pharyngeal edema, parosmia.

Skin: Aggravated condition, decreased therapeutic response, local edema, pain, paresthesia, pruritus, skin discoloration, and urticaria.

7 DRUG INTERACTIONS

No drug interaction studies have been performed with DENAVIR. Due to minimal systemic absorption of DENAVIR, systemic drug interactions are unlikely.

8 USE IN SPECIFIC POPULATIONS

8.1 Pregnancy

Risk Summary

DENAVIR is not absorbed systemically following topical administration and maternal use is not expected to result in fetal exposure to the drug.

8.2 Lactation

Risk Summary

DENAVIR is not absorbed systemically by the mother following topical administration and breastfeeding is not expected to result in exposure of the child to DENAVIR.

8.4 Pediatric Use

An open-label, uncontrolled trial with penciclovir cream 1% was conducted in 102 subjects, ages 12-17 years, with recurrent herpes labialis. The frequency of adverse events was generally similar to the frequency previously reported for adult patients. Safety and effectiveness in pediatric patients less than 12 years of age have not been established.

8.5 Geriatric Use

In 74 subjects ≥ 65 years of age, the adverse events profile was comparable to that observed in younger patients.

10 OVERDOSAGE

Since penciclovir is poorly absorbed following oral administration, adverse reactions related to penciclovir ingestion are unlikely. There is no information on overdose.

11 DESCRIPTION

DENAVIR (penciclovir) cream 1% contains penciclovir, an antiviral agent active against herpes viruses. DENAVIR is available for topical administration as a 1% white cream. Each gram of DENAVIR contains 10 mg of penciclovir and the following inactive ingredients: cetostearyl alcohol, mineral oil, polyoxyl 20 cetostearyl ether, propylene glycol, purified water and white petrolatum.

Chemically, penciclovir is known as 9-[4-hydroxy-3-(hydroxymethyl)butyl] guanine. Its molecular formula is C10H15N5O3; its molecular weight is 253.26. It is a synthetic acyclic guanine derivative and has the following structure:

Figure 1: Structural Formula of Penciclovir

Penciclovir is a white to pale yellow solid. At 20°C it has a solubility of 0.2 mg/mL in methanol, 1.3 mg/mL in propylene glycol, and 1.7 mg/mL in water. In aqueous buffer (pH 2) the solubility is 10.0 mg/mL. Penciclovir is not hygroscopic. Its partition coefficient in n-octanol/water at pH 7.5 is 0.024 (logP = -1.62).

12 CLINICAL PHARMACOLOGY

12.1 Mechanism of Action

Penciclovir is an antiviral agent active against alpha herpes viruses [see Microbiology (12.4)].

12.3 Pharmacokinetics

Measurable penciclovir concentrations were not detected in plasma or urine of healthy male volunteers (n=12) following single or repeat application of the 1% cream at a dose of 180 mg penciclovir daily (approximately 67 times the estimated usual clinical dose).

Pediatric Patients

The systemic absorption of penciclovir following topical administration has not been evaluated in patients < 18 years of age.

12.4 Microbiology

Mechanism of Action

Penciclovir has inhibitory activity against herpes simplex virus types 1 (HSV-1) and 2 (HSV-2). In cells infected with HSV-1 or HSV-2, the viral thymidine kinase phosphorylates penciclovir to a monophosphate form that, in turn, is converted by cellular kinases to the active form penciclovir triphosphate. Biochemical studies demonstrate that penciclovir triphosphate inhibits HSV DNA polymerase competitively with deoxyguanosine triphosphate. Consequently, α-herpes viral DNA synthesis and, therefore, replication are selectively inhibited. Penciclovir triphosphate has an intracellular half-life of 10 hours in HSV-1 and 20 hours in HSV-2 infected cells grown in culture. However, the clinical significance of the intracellular half-life is unknown.

Antiviral Activity

In cell culture studies, penciclovir has antiviral activity against the following herpes viruses: HSV-1 and HSV-2. The antiviral activity of penciclovir against wild type strains grown on human foreskin fibroblasts was assessed with a plaque reduction assay and staining with crystal violet 3 days post-infection for HSV. The median EC50 values of penciclovir against laboratory and clinical isolates of HSV-1 and HSV-2 were 2 μM (range 1.2 to 2.4 μM, n=7) and 2.6 μM (range 1.6 to 11 μM, n=6), respectively.

Resistance

In Cell Culture

Penciclovir-resistant HSV-1 and HSV-2 strains were isolated in cell culture. Penciclovir-resistant mutants of HSV resulted from mutations in the viral thymidine kinase (TK) and DNA polymerase (POL) genes. Frameshifts were commonly isolated and result in premature truncation of the HSV TK product with decreased enzymatic activity and consequent decreased susceptibility to penciclovir. Mutations in the viral TK gene may lead to complete loss of TK activity (TK negative), reduced levels of TK activity (TK partial), or alteration in the ability of viral TK to phosphorylate the drug without an equivalent loss in the ability to phosphorylate thymidine (TK altered). In cell culture, the following resistance-associated substitutions in TK of HSV-1 and HSV-2 were observed: HSV-1 TK G6C, F13L, H142Y, G200D, L205S, S254Stop, V267G, and T287M; HSV-2 TK G39E, F191L, E226K, and T288M. The median EC50 values observed in a plaque reduction assay with penciclovir resistant HSV-1 and HSV-2 were 69 μM (range 14 to 115 μM, n=6) and 46 μM (range 4 to > 395 μM, n=9), respectively.

Resistance and Cross-resistance in Clinical Isolates from HSV-Infected Patients

Clinical HSV-1 and HSV-2 isolates obtained from patients who failed treatment with acyclovir for their α-herpesvirus infections were evaluated for genotypic changes in the TK and POL genes. These HSV isolates had frameshift mutations leading to loss of thymidine kinase or had substitutions in the viral thymidine kinase and viral DNA polymerase. Phenotypic analysis of these clinical isolates confirmed resistance to penciclovir and acyclovir. These and other resistance-associated substitutions reported in the literature, or observed in clinical trials, are listed in Table 2. The list is not all inclusive and additional changes will likely be identified in HSV variants isolated from patients who fail penciclovir containing regimens. The possibility of viral resistance to penciclovir should be considered in patients who fail to respond or experience recurrent viral shedding during therapy.

Table 2: Summary of Known HSV TK and POL Amino Acid Substitutions Conferring Resistance to Acyclovir and Cross-Resistance to Penciclovir
HSV-1 | TK | G6C, R32H, R51W, Y53C/H, H58N, G59W, G61A, S74Stop, E83K, P84L, T103P, Q104Stop, D116N, M121R, I143V, R163H, L170P, Y172C, A174P, R176Q/W, Q185R, A189V, G200D, G206R, L208H, R216C, R220H, R222C/H, FS 224, Y239S, T245M, Q250Stop, S254Stop, R256W, Q261Stop, R281Stop, T287M, L315S, M322K, C336Y
HSV-2 | TK | G39E, R51W, Y53N, R221H, T288M
HSV-1 | POL | A657T, D672N, V715G, A719V, S724N, E798K, V813M, N815S, Y818C, G841S, R842S, F891C, V958L
HSV-2 | POL | -
Note: Many additional pathways to penciclovir resistance likely exist.

Cross-resistance has been observed among HSV isolates carrying foscarnet resistance-associated substitutions (Table 3).

Table 3: Summary of Known HSV-1 POL Amino Acid Substitutions Conferring Resistance to Foscarnet and Cross-Resistance to Penciclovir
HSV-1 | POL | D672N, S724N, E798K, V813M, Y818C, F891C, V958L

13 NONCLINICAL TOXICOLOGY

13.1 Carcinogenesis, Mutagenesis, Impairment of Fertility

In clinical trials, systemic drug exposure following topical administration of penciclovir cream was negligible, as the penciclovir content of all plasma and urine samples was below the limit of assay detection (0.1 mcg/mL and 10 mcg/mL, respectively). However, for the purpose of inter-species dose comparisons presented in the following sections, an assumption of 100% absorption of penciclovir from the topically applied product has been used. Based on the use of the maximal recommended topical dose of penciclovir of 0.05 mg/kg/day and an assumption of 100% absorption, the maximum theoretical plasma AUC0-24 hrs for penciclovir is approximately 0.129 mcg.hr/mL.

Carcinogenesis

Two-year carcinogenicity studies were conducted with famciclovir (the oral prodrug of penciclovir) in rats and mice. An increase in the incidence of mammary adenocarcinoma (a common tumor in female rats of the strain used) was seen in female rats receiving 600 mg/kg/day (approximately 395x the maximum theoretical human exposure to penciclovir following application of the topical product, based on area under the plasma concentration curve comparisons [24 hr. AUC]). No increases in tumor incidence were seen among male rats treated at doses up to 240 mg/kg/day (approximately 190x the maximum theoretical human AUC for penciclovir), or in male and female mice at doses up to 600 mg/kg/day (approximately 100x the maximum theoretical human AUC for penciclovir).

Mutagenesis

When tested in vitro, penciclovir did not cause an increase in gene mutation in the Ames assay using multiple strains of S. typhimurium or E. coli (at up to 20,000 mcg/plate), nor did it cause an increase in unscheduled DNA repair in mammalian HeLa S3 cells (at up to 5,000 mcg/mL). However, an increase in clastogenic responses was seen with penciclovir in the L5178Y mouse lymphoma cell assay (at doses ≥1000 mcg/mL) and, in human lymphocytes incubated in vitro at doses ≥250 mcg/mL. When tested in vivo, penciclovir caused an increase in micronuclei in mouse bone marrow following the intravenous administration of doses ≥500 mg/kg (≥810x the maximum human dose, based on body surface area conversion).

Impairment of Fertility

Testicular toxicity was observed in multiple animal species (rats and dogs) following repeated intravenous administration of penciclovir (160 mg/kg/day and 100 mg/kg/day, respectively, approximately 1155 and 3255x the maximum theoretical human AUC). Testicular changes seen in both species included atrophy of the seminiferous tubules and reductions in epididymal sperm counts and/or an increased incidence of sperm with abnormal morphology or reduced motility. Adverse testicular effects were related to an increasing dose or duration of exposure to penciclovir. No adverse testicular or reproductive effects (fertility and reproductive function) were observed in rats after 10 to 13 weeks dosing at 80 mg/kg/day, or testicular effects in dogs after 13 weeks dosing at 30 mg/kg/day (575 and 845x the maximum theoretical human AUC, respectively). Intravenously administered penciclovir had no effect on fertility or reproductive performance in female rats at doses of up to 80 mg/kg/day (260x the maximum human dose [BSA]).

There was no evidence of any clinically significant effects on sperm count, motility or morphology in 2 placebo-controlled clinical trials of Famvir® (famciclovir [the oral prodrug of penciclovir], 250 mg twice daily; n=66) in immunocompetent men with recurrent genital herpes, when dosing and follow-up were maintained for 18 and 8 weeks, respectively (approximately 2 and 1 spermatogenic cycles in the human).

14 CLINICAL STUDIES

DENAVIR was studied in two double-blind, placebo (vehicle)-controlled trials for the treatment of recurrent herpes labialis in which otherwise healthy adults were randomized to either DENAVIR or placebo. Therapy was to be initiated by the subjects within 1 hour of noticing signs or symptoms and continued for 4 days, with application of study medication every 2 hours while awake. In both studies, the mean duration of lesions was approximately one-half-day shorter in the subjects treated with DENAVIR (N=1,516) as compared to subjects treated with placebo (N=1,541) (approximately 4.5 days versus 5 days, respectively). The mean duration of lesion pain was also approximately one half-day shorter in the DENAVIR group compared to the placebo group.

16 HOW SUPPLIED/STORAGE AND HANDLING

DENAVIR is supplied in a 5 gram tube containing 10 mg of penciclovir per gram in a cream base, which is equivalent to 1% (w/w). The white cream is available as follows:

NDC 0378-9720-55
carton containing one 5 gram tube

Store at 20º to 25ºC (68º to 77ºF). [See USP Controlled Room Temperature].

17 PATIENT COUNSELING INFORMATION

Administration Instructions

Advise the patient that treatment should be started at the earliest sign of a cold sore (i.e. tingling, redness, itching, or bump). Inform the patient to apply the cream every 2 hours during waking hours for 4 days and to wash their hands with soap and water after using DENAVIR.

Denavir is a registered trademark of Denco Asset, LLC, a Mylan Company.

The brands listed are trademarks of their respective owners.

©2018 Mylan Pharmaceuticals Inc.

Manufactured for:
Mylan Pharmaceuticals Inc.
Morgantown, WV 26505 U.S.A.

Manufactured by:
Confab Laboratories Inc.
St-Hubert, Canada J3Y 3X3

Revised: 11/2018

301459-03
CON:PENCCR:R2

PRINCIPAL DISPLAY PANEL – 1%

NDC 0378-9720-55
Rx only

Denavir®
(penciclovir cream) 1%
For Topical Use Only

5 g (Net Wt.)

Each gram contains 10 mg penciclovir; inactive ingredients consist of cetomacrogol 1000
BP, cetostearyl alcohol, mineral oil, propylene glycol, purified water and white petrolatum.

Usual Dosage: See accompanying prescribing information.

To Open Tube: Unscrew cap, puncture aluminum seal with pointed end of cap.

Store at controlled room temperature 20° to 25°C (68° to 77°F).
[See USP Controlled Room Temperature.]

Denavir® is a registered trademark of Denco Asset, LLC, a Mylan Company
© 2018 Mylan Pharmaceuticals Inc.

Comments or Questions? Call 1-877-446-3679 (1-877-4-INFO-RX)

Manufactured in Canada for:
Mylan Pharmaceuticals Inc.
Morgantown, WV 26505 U.S.A.

CON:9720:55:1C:R1